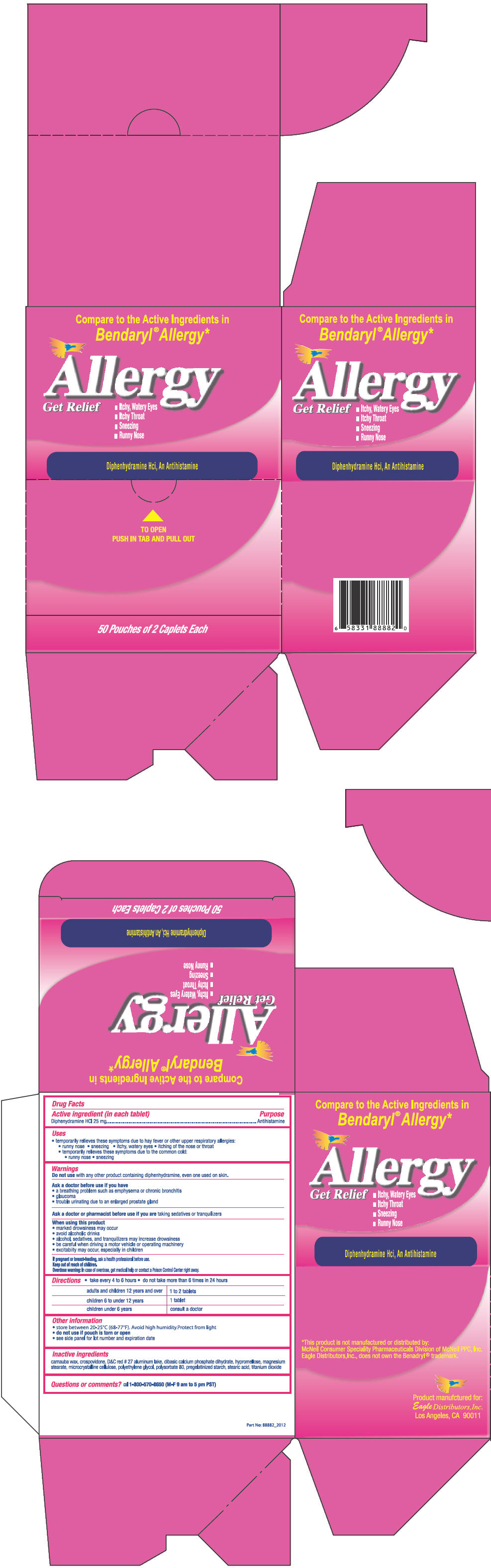 DRUG LABEL: Allergy Get Relief
NDC: 68737-223 | Form: TABLET
Manufacturer: Eagle Distributors,Inc.
Category: otc | Type: HUMAN OTC DRUG LABEL
Date: 20120611

ACTIVE INGREDIENTS: Diphenhydramine Hydrochloride 25 mg/1 1
INACTIVE INGREDIENTS: croscarmellose sodium; D&C Red No. 27; hypromelloses; lactose; magnesium stearate; cellulose, microcrystalline; polyethylene glycols; silicon dioxide; titanium dioxide

Allergy Get Relief

Drug Facts

Active ingredient (in each caplet)

Diphenhydramine HCl 25 mg

Purpose

Antihistamine

Uses

temporarily relieves these symptoms due to hay fever or other upper respiratory allergies:

- sneezing
- runny nose
- itchy, watery eyes
- itching of the nose or throat
- and these symptoms associated with the common cold:
  - sneezing
  - runny nose

Warnings

Do not use with any other products containing diphenhydramine, including one used on skin

Ask a doctor before use if you have

- a breathing problem such as emphysema or chronic bronchitis
- glaucoma or
- trouble urinating due to an enlarged prostate gland

Ask a doctor or pharmacist before use if you are taking sedatives or tranquilizers

When using this product

- marked drowsiness may occur
- avoid alcoholic beverages
- alcohol, sedatives, and tranquilizers may increase drowsiness
- be careful when driving a motor vehicle or operating machinery
- excitability may occur, especially in children

PREGNANCY OR BREAST FEEDING

If pregnant or breast-feeding, ask a health professional before use

Keep out of reach of children.

Overdose warning

In case of accidental overdose, contact a doctor or Poison Control Center immediately.

Directions

- take every 4 to 6 hours
- do not take more than 6 doses in 24 hours

Adults and children 12 years of age and over | 1 to 2 caplets
Children 6 to under 12 years | 1 caplet
Children under 6 years | Consult a doctor

Other information

- store between 20-25 C (68-77 F).Avoid high humidity. Protect from light
- do not use if pouch is torn or open
- see side panel for lot number and expiration date

Inactive ingredients

croscarmellose sodium, D&C Red #27, hydroxypropylmethyl cellulose, lactose, magnesium stearate, microcrystalline cellulose, polyethylene glycol, silicon dioxide, titanium dioxide. May contain polysorbate.

Questions or comments?

Call toll free 1-800-570-8650 (M-F 9 am to 5 pm PST)

*This product is not manufactured or distributed by McNeil Consumer Healthcare, distributor of Benadryl®

Product manufactured for:
Eagle Distributors,Inc.
Los Angeles, CA 90011

PRINCIPAL DISPLAY PANEL - 50 Pouch Carton

Compare to the Active Ingredients in
Bendaryl® Allergy*

Allergy
Get Relief

- Itchy, Watery Eyes
- Itchy Throat
- Sneezing
- Runny Nose

Diphenhydramine Hci, An Antihistamine